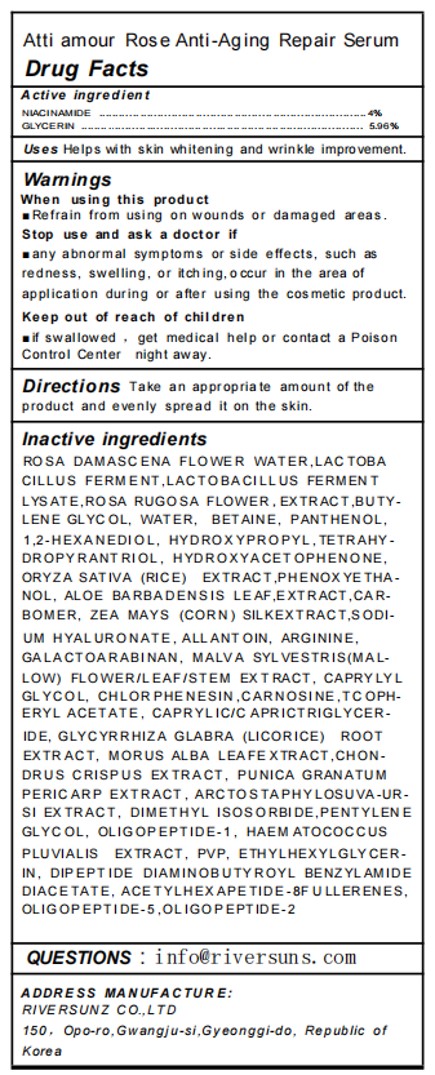 DRUG LABEL: Atti amour Rose Anti-Aging Repair Serum
NDC: 84601-002 | Form: LIQUID
Manufacturer: RIVER SUNZ co.,Ltd
Category: otc | Type: HUMAN OTC DRUG LABEL
Date: 20251106

ACTIVE INGREDIENTS: GLYCERIN 5.96 g/100 mL; NIACINAMIDE 4 g/100 mL
INACTIVE INGREDIENTS: ROSA RUGOSA FLOWER; ALLANTOIN; MORUS ALBA LEAF; HAEMATOCOCCUS PLUVIALIS; DIPEPTIDE DIAMINOBUTYROYL BENZYLAMIDE DIACETATE; ALOE VERA LEAF; ACETYL HEXAPEPTIDE-8; 1,2-HEXANEDIOL; CAPRYLYL GLYCOL; PENTYLENE GLYCOL; ARGININE; CARNOSINE; BIFIDOBACTERIUM ANIMALIS LACTIS; BUTYLENE GLYCOL; LACTOBACILLUS REUTERI F275 STRAIN; POMEGRANATE FRUIT RIND; CHONDRUS CRISPUS CARRAGEENAN; DIMETHICONE/VINYL DIMETHICONE CROSSPOLYMER (HARD PARTICLE); ALPHA-TOCOPHEROL ACETATE; WATER; CHLORPHENESIN; DIMETHYL ISOSORBIDE; CORN SILK; MEDIUM-CHAIN TRIGLYCERIDES; BETAINE; BUCKMINSTERFULLERENE; POVIDONE; MALVA SYLVESTRIS FLOWERING TOP; RICE GERM; GALACTOARABINAN; PHENOXYETHANOL; CARBOMER HOMOPOLYMER, UNSPECIFIED TYPE; PANTHENOL; HYDROXYPROPYL TETRAHYDROPYRANTRIOL; HYALURONATE SODIUM; ETHYLHEXYLGLYCERIN; HYDROLYZED WHEAT PROTEIN (ENZYMATIC, 3000 MW); GLYCYRRHIZA GLABRA; ARCTOSTAPHYLOS UVA-URSI WHOLE; ROSA DAMASCENA FLOWER OIL

84601-002 Atti amour Rose Anti-Aging Repair Serum

ACTIVE INGREDIENT

NIACINAMIDE 4%
GLYCERIN 5.96%

PURPOSE

Helps with skin whitening and wrinkle impro vement.

Keep out of reach of children
if swallowed , get medical help or contact a PoisonControl Center night away.

INDICATIONS AND USAGE

Uses Helps with skin whitening and wrinkle impro vement.

When using this product
Refrain from using on wounds or damaged areas.
Stop use and ask a doctor if
any abnormal symptoms or side effects, such asredness, swelling, or itching,o ccur in the area ofapplication during or after using the cosmetic product.
Keep out of reach of childrenm
if swallowed , get medical help or contact a PoisonControl Center night away.

DOSAGE AND ADMINISTRATION

Directions Take an appropriate amount of theproduct and evenly spread it on the skin.

STORAGE AND HANDLING

Store in a cool and shady place

INACTIVE INGREDIENT

LACTOBACILLUS FERMENT
ROSA DAMASCENA FLOWER WATER
LACTOBACILLUS FERMENT LYSATE
ROSA RUGOSA FLOWER EXTRACT
HYDROXYACETOPHENONE
1,2-HEXANEDIOL
BUTYLENE GLYCOL
ORYZA SATIVA (RICE) EXTRACT
ZEA MAYS (CORN) SILK EXTRACT
MALVA SYLVESTRIS (MALLOW) FLOWER/LEAF/STEM EXTRACT
ALOE BARBADENSIS LEAF EXTRACT
WATER
BETAINE
GALACTOARABINAN
PHENOXYETHANOL
CAPRYLYL GLYCOL
CHLORPHENESIN
PANTHENOL
HYDROXYPROPYL TETRAHYDROPYRANTRIOL
CARBOMER
ALLANTOIN
SODIUM HYALURONATE
ARGININE
CARNOSINE
OLIGOPEPTIDE-1
OLIGOPEPTIDE-5
OLIGOPEPTIDE-2
HAEMATOCOCCUS PLUVIALIS EXTRACT
CAPRYLIC/CAPRIC TRIGLYCERIDE
GLYCYRRHIZA GLABRA (LICORICE) ROOT EXTRACT
MORUS ALBA LEAF EXTRACT
PUNICA GRANATUM PERICARP EXTRACT
ARCTOSTAPHYLOS UVA-URSI EXTRACT
CHONDRUS CRISPUS EXTRACT
PENTYLENE GLYCOL
DIPEPTIDE DIAMINOBUTYROYL BENZYLAMIDE DIACETATE
ACETYL HEXAPEPTIDE-8
DIMETHYL ISOSORBIDE
ETHYLHEXYLGLYCERIN
TOCOPHERYL ACETATE
FULLERENES
PVP